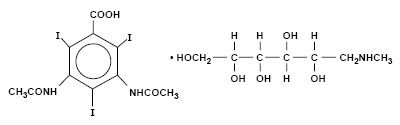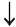 DRUG LABEL: Unknown
Manufacturer: Amersham Health Inc.
Category: prescription | Type: HUMAN PRESCRIPTION DRUG LABELING
Date: 20070803

HYPAQUE-CYSTO™
(Diatrizoate Meglumine Injection, USP)
30%

Sterile Aqueous Injection

NOT FOR INTRATHECAL USE

Not For Intravascular Use

For Retrograde Cystourethrography

Rx ONLY

DESCRIPTION

HYPAQUE-CYSTO, brand of diatrizoate meglumine, is a water-soluble radiopaque diagnostic medium. It is a triiodinated benzoic acid derivative. It is constituted as a radiopaque iodinated anion (diatrizoate) and a radiolucent cation (meglumine). It is a colorless, microcrystalline solid which is readily soluble in water.

HYPAQUE-CYSTO is a sterile aqueous solution containing 30 g (w/v) of the meglumine salt of diatrizoic acid per 100 mL aqueous solution. The sterile solution is clear and colorless to pale yellow. The pH is adjusted between 6.5 and 7.7 with hydrochloric acid, or diatrizoic acid, or meglumine. It does not contain an antibacterial preservative. It is relatively thermostable and may be autoclaved. Edetate calcium disodium 1:10,000 has been added as a sequestering stabilizing agent. Each 1 mL contains approximately 141 mg of organically bound iodine.

It has an osmolality of 633 mosm/kg (determined by VPO) and is hypertonic to blood.

The viscosity of the solution is 1.94 cp at 25°C and 1.42 cp at 37°C.

HYPAQUE-CYSTO is a 30 percent solution of 1-Deoxy-l (methylamino)-D-glucitol 3,5-diacetamido-2,4,6-triiodobenzoate (C11H9I3N2O4 • C7H17NO5) with a molecular weight of 809.13, and has the following structural formula:

CLINICAL PHARMACOLOGY

Retrograde introduction of HYPAQUE-CYSTO solution provides radiopacity of the contents of the urinary bladder. When used during micturation as a function test, it also opacifies the bladder neck and lower urinary tract. Continuous fluoroscopic and monitoring of urinary bladder contractions will demonstrate cystoureteric reflux and its extent, if present.

HYPAQUE-CYSTO is not absorbed from the urinary tract to any extent (< 2°), therefore, systemic effects are rare. However, pyelorenal intravasation (especially in patients with ureteric reflux) can occur. Therefore, the potential for adverse effects, such as occur with intravascular use, are possible.

At physiologic pH, the water-soluble contrast media are completely dissociated into a radiopaque anion and a solubilizing cation.

EXCRETION

HYPAQUE-CYSTO which gains inadvertent intravascular entry is not metabolized but excreted unchanged in the urine, each diatrizoate molecule remaining "obligated" to its cation moiety.

Diatrizoate solutions may be excreted either through the kidneys or the liver. These two excretory pathways are not mutually exclusive, but the main route of excretion seems to be governed by the affinity of the contrast medium for serum albumin. From 0% to 10% of diatrizoate meglumine is bound to serum protein.

Diatrizoate salts are excreted unchanged predominantly through the kidneys by glomerular filtration. The amount excreted during any period of time is determined by the filtered load; ie, the product of plasma contrast media concentration and glomerular filtration rate.

The liver and small intestine provide the major alternate route of excretion for diatrizoate. In patients free of severe renal disease, the fecal recovery is less than 2 percent. In patients with severe renal impairment the excretion of these contrast media through the gallbladder and into the small intestine sharply increases; up to 20 percent in the feces in 48 hours.

Saliva is a minor secretory pathway for injectable radiopaque diagnostic agents. In patients with normal renal function, minimal amounts of contrast media are secreted unchanged.

PREGNANCY AND LACTATION

Diatrizoate meglumine crosses the human placental barrier by simple diffusion and appears to enter fetal tissues passively. No apparent harm to the fetus occurs. Procedures including radiation involve a certain risk related to the exposure of the fetus.

Diatrizoate solutions are excreted unchanged in human milk.

INDICATIONS AND USAGE

HYPAQUE-CYSTO is indicated for retrograde cystourethrography in adult and pediatric patients.

CONTRAINDICATIONS

HYPAQUE-CYSTO has no absolute contraindication in its recommended use.

WARNINGS

SEVERE ADVERSE EVENTS—INADVERTENT INTRATHECAL USE

Serious adverse reactions have been reported due to the inadvertent intrathecal administration of iodinated contrast media that are not indicated for intrathecal use. These serious adverse reactions include: death, convulsions, cerebral hemorrhage, coma, paralysis, arachnoiditis, acute renal failure, cardiac arrest, seizures, rhabdomyolysis, hyperthermia, and brain edema. Special attention must be given to insure that this drug product is not administered intrathecally.

Ionic iodinated contrast media inhibit blood coagulation, in vitro, more than nonionic contrast media. Nonetheless, it is prudent to avoid prolonged contact of blood with syringes containing ionic contrast media.

Serious, rarely fatal, thromboembolic events causing myocardial infarction and stroke have been reported during angiographic procedures with both ionic and nonionic contrast media. Therefore, meticulous intravascular administration technique is necessary, particularly during angiographic procedures, to minimize thromboembolic events. Numerous factors, including length of procedure, catheter and syringe material, underlying disease state and concomitant medications may contribute to the development of thromboembolic events. For these reasons, meticulous angiographic techniques are recommended including close attention to guidewire and catheter manipulation, use of manifold systems and/or three-way stopcocks, frequent catheter flushing with heparinized saline solutions and minimizing the length of the procedure. The use of plastic syringe in place of glass syringes has been reported to decrease but not eliminate the likelihood of in vitro clotting.

Serious or fatal reactions have been associated with the vascular entry of radiopaque media. It is important that a course of action be carefully planned in advance for the treatment of possible serious reactions.

PRECAUTIONS

General

Diagnostic procedures which involve the use of radiopaque diagnostic agents should be carried out under the direction of personnel with the prerequisite training and with a thorough knowledge of the particular procedure to be performed. Appropriate facilities should be available for the management of any complication of the procedure, as well as for emergency treatment of severe reactions to the contrast agent itself. Competent personnel and emergency facilities should be available for at least 30 to 60 minutes since severe delayed reactions have occurred (See ADVERSE REACTIONS).

The possibility of a reaction, including serious, life-threatening, fatal, anaphylatic or cardiovascular reactions should always be considered (see ADVERSE REACTIONS). It is of utmost importance that a course of action be carefully planned in advance for immediate treatment of serious reactions, and that adequate and appropriate personnel be readily available in case of any reaction.

ALLERGIC HISTORY

Before injecting a contrast medium, the patient should be questioned for a history of allergy. A positive history does not arbitrarily contraindicate the use of a contrast agent where a diagnostic procedure is considered essential, but caution should be exercised (see ADVERSE REACTIONS).

The possibility of an idiosyncratic reaction in susceptible patients should always be considered (see ADVERSE REACTIONS). The susceptible population includes patients with a history of a previous reaction to a contrast media, patients with a known sensitivity to iodine per se, and patients with known clinical hypersensitivity (ie, bronchial asthma, hay fever, and food allergies).

Premedication with antihistamines or corticosteroids to avoid or minimize possible allergic reactions in such patients should be considered. Recent reports indicate that such pretreatment does not prevent serious life-threatening reactions, but may reduce both their incidence and severity.

TEST DOSE

The occurrence of severe idiosyncratic reactions has prompted the use of several pretesting methods. However, pretesting cannot be relied upon to predict severe reactions and may itself be hazardous for the patient. It is suggested that a thorough medical history with emphasis on allergy and hypersensitivity, prior to the injection of any contrast media, may be more accurate than pretesting in predicting adverse reactions.

Information for Patients

Patients receiving injectable radiopaque diagnostic agents should be instructed to:

- Inform the physician if they are pregnant (see CLINICAL PHARMACOLOGY).
- Inform the physician if they are allergic to any drugs, food, or if they have had any reactions to previous injections of dyes used for x-ray procedures (see PRECAUTIONS).

Drug/Laboratory Test Interactions

Under certain circumstances (pH, temperature, concentrations, time), diatrizoate solutions are incompatible with promethazine hydrochloride, diphenhydramine hydrochloride, brompheniramine maleate, or papaverine hydrochloride solutions.

BENADRYL®, brand of diphenhydramine hydrochloride, may cause precipitation when mixed in the same syringe with HYPAQUE-CYSTO.

Although interference with these laboratory tests have not been reported following cystography absorption (from the bladder or by pyelorenal back flow), they have occurred following direct intravenous injection. Therefore, if any of these studies, which might be affected by contrast media are indicated, it is recommended that they be performed prior to administration of the contrast medium or two or more days afterwards.

Diatrizoate salts interfere with several laboratory urine and blood tests.

Blood Tests

Coagulation: Diatrizoate salts significantly inhibit all stages of coagulation. The fibrinogen concentration, Factors V, VII, and VIII are decreased. Prothrombin time and thromboplastin time are increased.

Platelet aggregation: High levels of plasma and diatrizoate meglumine inhibit platelet aggregation.

Serum calcium: Diatrizoate salts may decrease serum calcium levels. However, this depletion of serum calcium may also be the result of the addition of chelating agents (edetate disodium) in the preparation of certain contrast media.

Red cell counts: Transitory decreases in red cell counts. Technetium-99m-RBC labeling interference.

Leukocyte counts: Decrease.

Urea nitrogen (BUN): Transitory increase (see CLINICAL PHARMACOLOGY).

Serum creatinine: Transitory increase.

Urine Tests

Urine osmolarity and specific gravity. Decreased due to induced diuresis.

Urine cultures. Diatrizoate in urine cultures may inhibit bacterial growth.

Thyroid Function Tests

Protein-bound iodine (PBI) and total serum organic iodine: Transient increase of both tests following cystography and retrograde pyelography have been noticed. The results of PBl and radioactive iodine uptake studies which depend on iodine estimations will not accurately reflect thyroid function for up to 16 days following administration of iodinated media. However, thyroid function tests not depending on iodine estimations, eg, T3 resin uptake or free thyroxine assays are not affected.

Carcinogenesis, Mutagenesis, Impairment of Fertility

Long-term studies in animals have not been performed in order to evaluate carcinogenic potential, mutagenesis, or whether HYPAQUE-CYSTO can affect fertility in males or females.

Pregnancy Category C

Animal reproduction studies have not been conducted with diatrizoate meglumine. It is also not known whether it can cause fetal harm when administered to a pregnant woman or can affect reproduction capacity. Therefore, diatrizoate meglumine should be given to a pregnant woman only if clearly needed.

Labor and Delivery

It is not known whether use of these contrast agents during labor or delivery has immediate or delayed adverse effects on the fetus, prolongs the duration of labor or increases the likelihood that forceps delivery or other obstetrical intervention or resuscitation of the newborn will be necessary.

Nursing Mothers

Diatrizoate salts are excreted unchanged in human milk. Because of the potential adverse reactions, although it has not been established that serious adverse reactions occur in nursing infants, caution should be exercised when these contrast media are administered to a nursing woman.

ADVERSE REACTIONS

Not For Intravascular Use

Because inadvertent intravascular entry of HYPAQUE-CYSTO is possible during urethrocystography (bladder absorption or pyelorenal back flow), the occurrence of systemic adverse effects is possible. However, the relative incidence and severity of the following reactions refer only to experience with direct intravascular injection.

Approximately 95 percent of adverse reactions accompanying the intravascular use of diatrizoate salts are of mild to moderate severity. However, life-threatening reactions and fatalities, mostly of cardiovascular origin, have occurred.

Adverse reactions to injectable contrast media fall into two categories: chemotoxic reactions and idiosyncratic reactions.

Chemotoxic reactions result from the physicochemical properties of the contrast media, the dose, and the speed of injection. All hemodynamic disturbances and injuries to organs or vessels perfused by the contrast medium are included in this category.

Idiosyncratic reactions include all other reactions. They occur more frequently in patients 20 to 40 years old. Idiosyncratic reactions may or may not be dependent on the amount of dose injected, the speed of injection, the mode of injection, and the radiographic procedure. Idiosyncratic reactions are subdivided into minor, intermediate, and severe. The minor reactions are self-limited and of short duration; the severe reactions are life-threatening and treatment is urgent and mandatory.

The reported incidence of adverse reactions to contrast media in patients with a history of allergy are twice that of the general population. Patients with a history of previous reactions to a contrast medium are three times more susceptible than other patients. However, sensitivity to contrast media does not appear to increase with repeated examinations.

Most adverse reactions to injectable contrast media appear within one to three minutes after the start of injection, but delayed reactions may occur.

Adverse reactions are grouped by organ system and listed below by decreasing order of occurrence and with an approximate incidence of occurrence. Significantly more severe reactions are listed before the other reactions regardless of frequency.

Greater Than 1 in 100 Patients

Body as a Whole: Reported incidences of death range from 6.6 per 1 million (0.00066 percent) to 1 in 10,000 patients (0.01 percent). Most deaths occur during injection or 5 to 10 minutes later, the main feature being cardiac arrest with cardiovascular disease as the main aggravating factor.

Isolated reports of hypotensive collapse and shock following urography are found in the literature. The incidence of shock is estimated to occur in 1 out of 20,000 (0.005 percent) patients.

Cardiovascular System: The most frequent adverse reaction to diatrizoate salts is vasodilation (feeling of warmth). The estimated incidence is 49 percent.

Digestive System: Nausea 6 percent, vomiting 3 percent.

Nervous System: Paresthesia 6 percent, dizziness 5 percent.

Respiratory System: Rhinitis 1 percent, increased cough 2 percent.

Skin and Appendages: Urticaria 1 percent.

Pain at the injection site is estimated to occur in about 12 percent of the patients undergoing urography. Pain is usually due to extravasation.

Painful hot erythematous swelling above the venipuncture site was estimated to occur in more than 1 percent of the patients undergoing phlebography.

Special Senses: Perversion of taste 11 percent.

Urogenital System: Osmotic nephrosis of the proximal tubular cells is estimated to occur in 23 percent of patients following excretory urography.

Less Than 1 in 100 Patients

Other infrequently reported reactions without accompanying incidence rates are listed below, grouped by organ system.

Body as a Whole: Malaria relapse, uremia, high creatinine and BUN (see PRECAUTIONS-Drug/Laboratory Test Interactions), thrombocytopenia, leukopenia, and anemia.

Cardiovascular System: Cerebral hematomas, hemodynamic disturbances, sinus bradycardia, transient electrocardiographic abnormalities, ventricular fibrillation, petechiae, chest pain, and cardiac arrest.

Digestive System: Severe unilateral or bilateral swelling of the parotid and submaxillary glands.

Nervous System: Convulsions, paralysis, and coma.

Respiratory System: Asthma, dyspnea, laryngeal edema, pulmonary edema, and bronchospasm.

Skin and Appendages: Skin necrosis.

Special Senses: Bilateral ocular irritation, lacrimation, itching, conjunctival chemosis, infection, and conjunctivitis.

Urogenital: Renal failure, pain.

DOSAGE AND ADMINISTRATION

After the bladder is emptied, HYPAQUE-CYSTO is gently instilled without force, often beyond the first desire to micturate, but not beyond the point of urgency or mild discomfort. The volume required to fill the bladder to slightly less than capacity may vary from patient to patient.

Bladder capacity in normal adults is generally 200 mL to 300 mL, and rarely, up to 600 mL. Capacity at birth is 20 mL to 50 mL, and increases about 400 percent in the first year. In children 3 to 5 years old, bladder capacity is 150 mL to 180 mL. In children older than 8 years, it is in the low adult range.

In disease, bladder capacity in adults may vary from 50 mL in a hypertonic reflex bladder to over 1000 mL in an atonic or sensory paralytic bladder or chronic lower urinary tract obstruction.

Repeat examination may be required to detect reflux, or in function studies.

The concentration varies with technique and equipment used. HYPAQUE-CYSTO may be diluted with sterile water or 5 percent dextrose solution, as indicated in the following table. A 10 percent solution is isotonic.

STANDARD PACKAGE (250 mL of HYPAQUE-CYSTO in 500 mL bottle)
TO MAKE |  | ADD | FINAL SOLUTION CONTAINS
Final conc. | Final volume | Sterile water or 5% dextrose solution | Iodine
30% | 250 mL | _ | 141 mg/mL
25% | 300 mL | 50 mL | 118 mg/mL
21.4% | 350 mL | 100 mL | 101 mg/mL
20% | 375 mL | 125 mL | 94 mg/mL
18.8% | 400 mL | 150 mL | 88 mg/mL
16.7% | 450 mL | 200 mL | 78 mg/mL
15% | 500 mL | 250 mL | 71 mg/mL

Note: To achieve the following concentrations some of the contrast agent must be removed prior to dilution.

TO MAKE |  | REMOVE | ADD | FINAL SOLUTION CONTAINS
Final conc. | Final volume |  | Sterile water or 5% dextrose solution | Iodine
12% | 500 mL | 50 mL | 300 mL | 56 mg/mL
12% | 375 mL | 100 mL | 225 mL | 56 mg/mL
10% | 450 mL | 100 mL | 300 mL | 47 mg/mL

Dilution and withdrawal of the contrast agent should be accomplished under aseptic conditions with sterile syringes. The solution should be inspected visually for particulate matter and discoloration prior to administration.

HOW SUPPLIED

STANDARD PACKAGE

Calibrated 500 mL dilution bottles containing 250 mL HYPAQUE-CYSTO; rubber stoppered, with hangers, inner removable seal and screw neck. Box of 10 (NDC 0407-0734-10)

Protect from light. Contains no preservatives, therefore, discard any unused portion remaining in the container.

Store at 15°C to 30°C (59°F to 86°F).

Distributed by Amersham Health Inc.
Princeton, NJ 08540

Printed in USA

Revised February 2003
HNC-3D